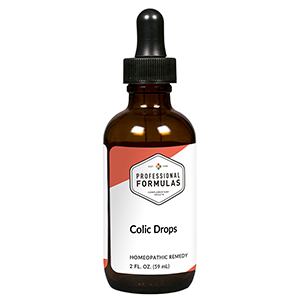 DRUG LABEL: Colic Drops
NDC: 63083-2155 | Form: LIQUID
Manufacturer: Professional Complementary Health Formulas
Category: homeopathic | Type: HUMAN OTC DRUG LABEL
Date: 20190815

ACTIVE INGREDIENTS: BRYONIA ALBA ROOT 4 [hp_X]/59 mL; LYCOPODIUM CLAVATUM SPORE 4 [hp_X]/59 mL; STRYCHNOS NUX-VOMICA SEED 4 [hp_X]/59 mL; CITRULLUS COLOCYNTHIS FRUIT PULP 6 [hp_X]/59 mL; ALUMINUM OXIDE 12 [hp_X]/59 mL; MERCURIC CHLORIDE 12 [hp_X]/59 mL; LEAD 12 [hp_X]/59 mL; SULFUR 12 [hp_X]/59 mL; LACHESIS MUTA VENOM 30 [hp_X]/59 mL; CASANTHRANOL 30 [hp_X]/59 mL; SENNA LEAF 30 [hp_X]/59 mL
INACTIVE INGREDIENTS: ALCOHOL; WATER

C155

ACTIVE INGREDIENTS

Bryonia 4X
Lycopodium clavatum 4X
Nux vomica 4X
Colocynthis 6X
Alumina 12X
Mercurius corrosivus 12X
Plumbum aceticum 12X
Sulphur 12X
Lachesis mutus 30X
Rhamnus purshiana 30X
Senna 30X

QUESTIONS

Professional Formulas

PO Box 2034 Lake Oswego, OR 97035

INDICATIONS

For temporary relief of irritability or abdominal tenderness, minor pain, or cramping.*

PURPOSE

*Claims based on traditional homeopathic practice, not accepted medical evidence. Not FDA evaluated.

WARNINGS

Consult a doctor if condition worsens or if symptoms persist. Keep out of the reach of children. In case of overdose, get medical help or contact a poison control center right away. If pregnant or breastfeeding, ask a healthcare professional before use.

Keep out of the reach of children.

PREGNANCY OR BREAST FEEDING

If pregnant or breastfeeding, ask a healthcare professional before use.

DIRECTIONS

Place drops under tongue 30 minutes before/after meals. Adults and children 12 years and over: Take 10 drops up to 3 times per day. Consult a physician for use in children under 12 years of age.

OTHER INFORMATION

Tamper resistant. If seal is broken, do not use. After opening, close container tightly and store at room temperature away from heat.

INACTIVE INGREDIENTS

10% ethanol, purified water, 8% vegetable glycerin (from soy).

LABEL

Est 1985

Professional Formulas

Complementary Health

Colic Drops

Homeopathic Remedy

2 FL. OZ. (59 mL)